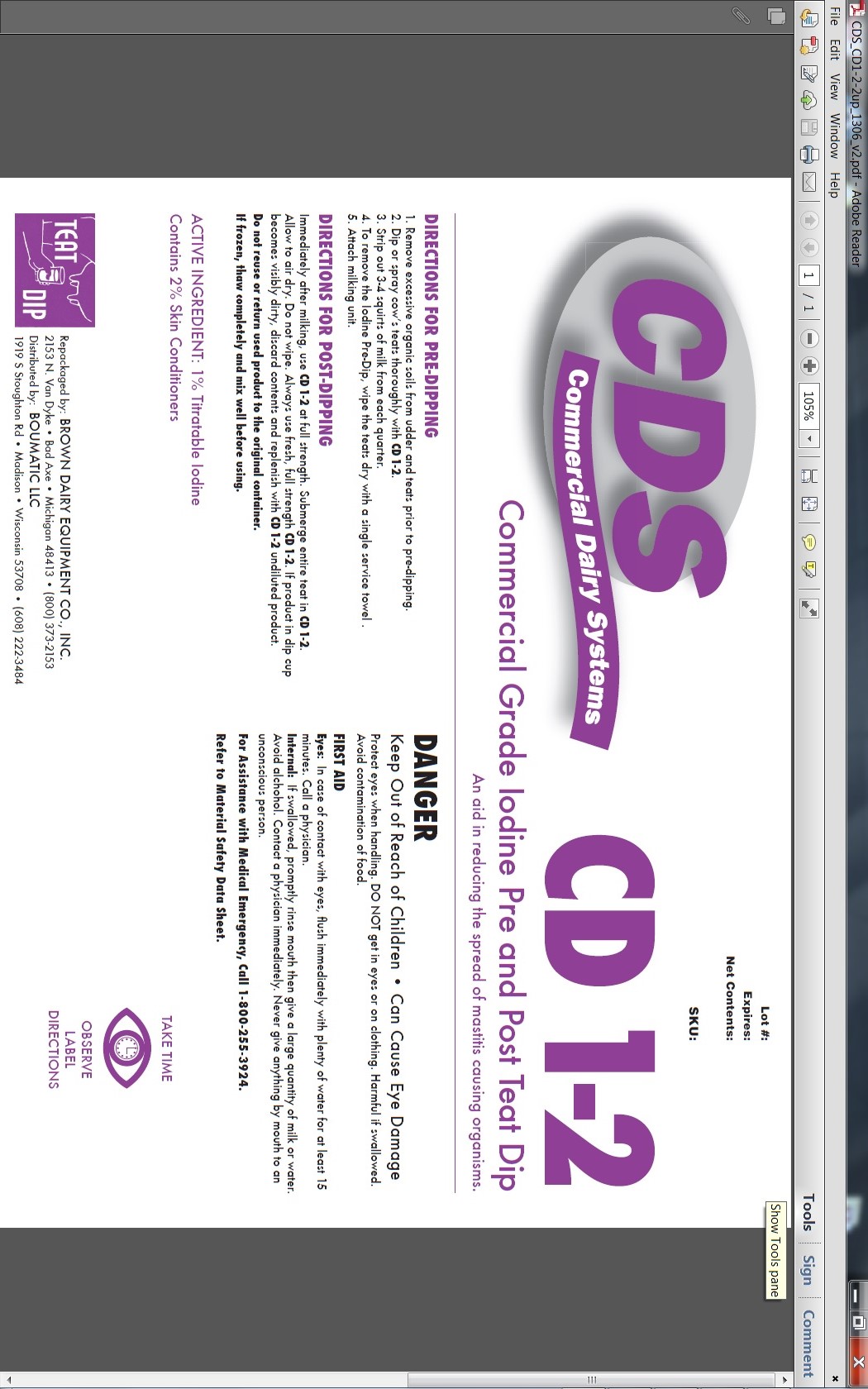 DRUG LABEL: CD 1-2
NDC: 48106-1191 | Form: LIQUID
Manufacturer: BouMatic, LLC
Category: animal | Type: OTC ANIMAL DRUG LABEL
Date: 20120101

ACTIVE INGREDIENTS: IODINE 100 g/10 L

CD 1-2

INDICATIONS AND USAGE

Commercial Grade Iodine Pre-dip

An aid in reducing the spread of mastitis causing organisms.

DIRECTIONS FOR PRE-DIPPING
1. Remove excessive organic soils from udder and teats prior to pre-dipping.
2. Dip or spray cow’s teats thoroughly with CD 1-2.
3. Strip out 3-4 squirts of milk from each quarter.
4. To remove the Iodine Pre-Dip, wipe the teats dry with a single service towel .
5. Attach milking unit.

DIRECTIONS FOR POST-DIPPING
Immediately after milking, use CD 1-2 at full strength. Submerge entire teat in CD 1-2.
Allow to air dry. Do not wipe. Always use fresh, full strength CD 1-2. If product in dip cup becomes visibly dirty, discard contents and replenish with CD 1-2 undiluted product.
Do not reuse or return used product to the original container.
If frozen, thaw completely and mix well before using.

ACTIVE INGREDIENT: 1% Titratable Iodine

Contains 2% Skin Conditioners

PRECAUTIONS

DANGER
Keep Out of Reach of Children • Can Cause Eye Damage
Protect eyes when handling. DO NOT get in eyes or on clothing. Harmful if swallowed.
Avoid contamination of food.
FIRST AID
Eyes: In case of contact with eyes, flush immediately with plenty of water for at least 15 minutes. Call a physician.
Internal: If swallowed, promptly rinse mouth then give a large quantity of milk or water. Avoid alchohol. Contact a physician immediately. Never give anything by mouth to an unconscious person.
For Assistance with Medical Emergency, Call 1-800-255-3924.
Refer to Material Safety Data Sheet.

PACKAGE LABEL

Enter section text here